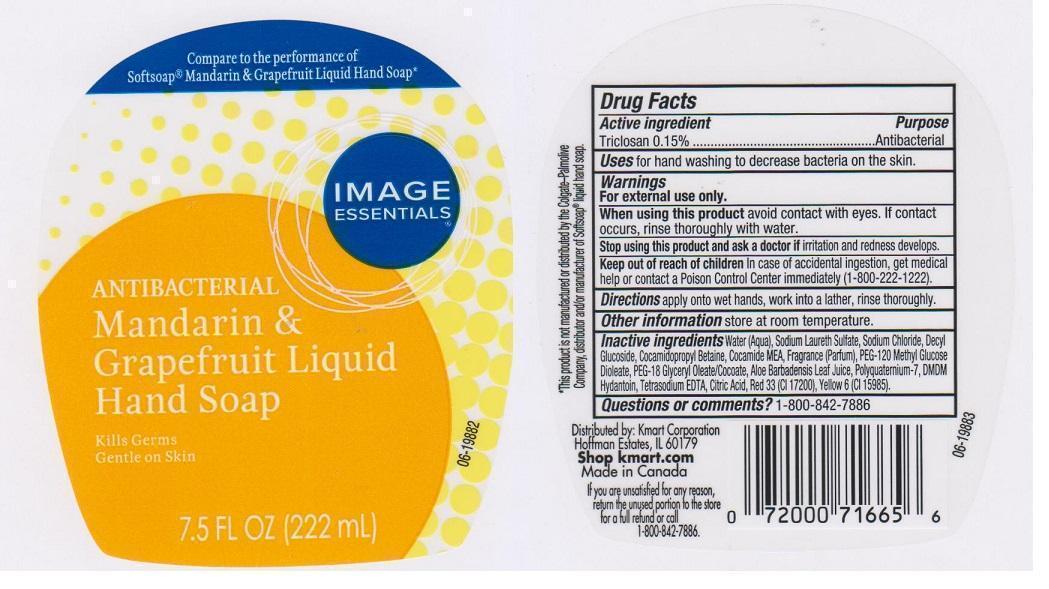 DRUG LABEL: IMAGE ESSENTIALS
NDC: 49738-015 | Form: LIQUID
Manufacturer: KMART CORPORATION
Category: otc | Type: HUMAN OTC DRUG LABEL
Date: 20141124

ACTIVE INGREDIENTS: TRICLOSAN 1.5 mg/1 mL
INACTIVE INGREDIENTS: WATER; SODIUM LAURETH SULFATE; SODIUM CHLORIDE; DECYL GLUCOSIDE; COCAMIDOPROPYL BETAINE; COCO MONOETHANOLAMIDE; PEG-120 METHYL GLUCOSE DIOLEATE; PEG-18 GLYCERYL OLEATE/COCOATE; ALOE VERA LEAF; POLYQUATERNIUM-7 (70/30 ACRYLAMIDE/DADMAC; 1600000 MW); DMDM HYDANTOIN; EDETATE SODIUM; CITRIC ACID MONOHYDRATE; D&C RED NO. 33; FD&C YELLOW NO. 6

DRUG FACTS

ACTIVE INGREDIENT

TRICLOSAN 0.15%

PURPOSE

ANTIBACTERIAL

USES

FOR HAND WASHING TO DECREASE BACTERIA ON THE SKIN

WARNINGS

FOR EXTERNAL USE ONLY

WHEN USING THIS PRODUCT

AVOID CONTACT WITH EYES. IF CONTACT OCCURS, RINSE THOROUGHLY WITH WATER

STOP USING THIS PRODUCT AND ASK A DOCTOR IF

IRRITATION AND REDNESS DEVELOPS

KEEP OUT OF REACH OF CHILDREN

IN CASE OF ACCIDENTAL INGESTION, GET MEDICAL HELP OR CONTACT A POISON CONTROL CENTER IMMEDIATELY (1-800-222-1222)

DIRECTIONS

APPLY ONTO WET HANDS, WORK INTO A LATHER, RINSE THOROUGHLY

OTHER INFORMATION

STORE AT ROOM TEMPERATURE

INACTIVE INGREDIENTS

WATER (AQUA), SODIUM LAURETH SULFATE, SODIUM CHLORIDE, DECYL GLUCOSIDE, COCAMIDOPROPYL BETAINE, COCAMIDE MEA, FRAGRANCE (PARFUM), PEG-120 METHYL GLUCOSE DIOLEATE, PEG-18 GLYCERYL OLEATE/COCOATE, ALOE BARBADENSIS LEAF JUICE, POLYQUATERNIUM-7, DMDM HYDANTOIN, TETRASODIUM EDTA, CITRIC ACID, RED 33 (CI 17200), YELLOW 6 (CI 15985)

QUESTIONS OR COMMENTS?

1-800-842-7886